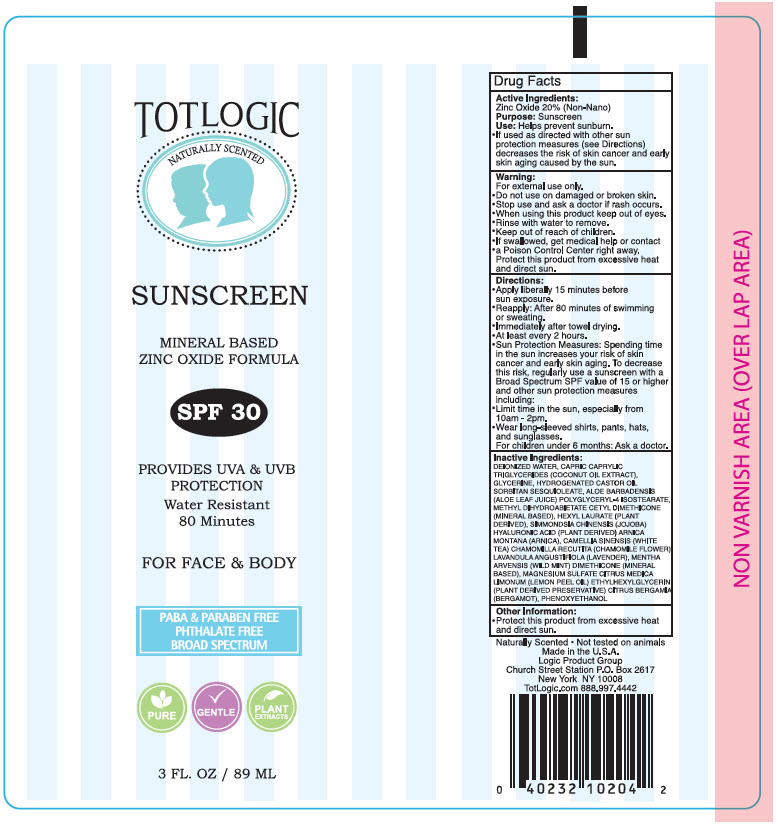 DRUG LABEL: TotLogic Sunscreen SPF 30
NDC: 71507-001 | Form: LOTION
Manufacturer: Logic Product Group LLC
Category: otc | Type: HUMAN OTC DRUG LABEL
Date: 20190829

ACTIVE INGREDIENTS: Zinc Oxide 200 mg/1 mL
INACTIVE INGREDIENTS: WATER; GLYCERIN; HYDROGENATED CASTOR OIL; SORBITAN SESQUIOLEATE; ALOE; POLYGLYCERYL-4 ISOSTEARATE; METHYL DIHYDROABIETATE; HEXYL LAURATE; ARNICA MONTANA; WHITE TEA; DIMETHICONE; MAGNESIUM SULFATE, UNSPECIFIED FORM; LEMON OIL; ETHYLHEXYLGLYCERIN; BERGAMOT OIL; PHENOXYETHANOL

TotLogic Sunscreen SPF 30

Drug Facts

Active Ingredients

Zinc Oxide 20% (Non-Nano)

Purpose

Sunscreen

Use

Helps prevent sunburn.

If used as directed with other sun protection measures (see Directions) decreases the risk of skin cancer and early skin aging caused by the sun.

Warning

For external use only

Do not use on damaged or broken skin.

Stop use and ask a doctor if rash occurs.

When using this product keep out of eyes.

Rinse with water to remove.

Keep out of reach of children. If swallowed, get medical help or contact a Poison Control Center right away.

STORAGE AND HANDLING

Protect this product from excessive heat and direct sun.

Directions

Apply liberally 15 minutes before sun exposure.

Reapply: After 80 minutes of swimming or sweating.

Immediately after towel drying. At least every 2 hours.

Sun Protection Measures

Spending time in the sun increases your risk of skin cancer and early skin aging. To decrease this risk, regularly use a sunscreen with a Broad Spectrum SPF value of 15 or higher and other sun protection measures including:

Limit time in the sun, especially from 10am - 2pm.

Wear long-sleeved shirts, pants, hats, and sunglasses.

For children under 6 months: Ask a doctor.

Inactive Ingredients

DEIONIZED WATER, CAPRIC CAPRYLIC TRIGLYCERIDES (COCONUT OIL EXTRACT), GLYCERINE, HYDROGENATED CASTOR OIL SORBITAN SESQUIOLEATE, ALOE BARBADENSIS (ALOE LEAF JUICE) POLYGLYCERYL-4 ISOSTEARATE, METHYL DIHYDROABIETATE CETYL DIMETHICONE (MINERAL BASED), HEXYL LAURATE (PLANT DERIVED), SIMMONDSIA CHINENSIS (JOJOBA) HYALURONIC ACID (PLANT DERIVED) ARNICA MONTANA (ARNICA) , CAMELLIA SINENSIS (WHITE TEA) CHAMOMILLA RECUTITA (CHAMOMILE FLOWER) LAVANDULA ANGUSTIFIOLA (LAVENDER), MENTHA ARVENSIS (WILD MINT) DIMETHICONE (MINERAL BASED), MAGNESIUM SULFATE CITRUS MEDICA LIMONUM (LEMON PEEL OIL) ETHYLHEXYLGLYCERIN (PLANT DERIVED PRESERVATIVE) CITRUS BERGAMIA (BERGAMOT), PHENOXYETHANOL

Other Information

Protect this product from excessive heat and direct sun.

PRINCIPAL DISPLAY PANEL - 89 ML Tube Label

TOTLOGIC

NATURALLY SCENTED

SUNSCREEN

MINERAL BASED
ZINC OXIDE FORMULA

SPF 30

PROVIDES UVA & UVB
PROTECTION

Water Resistant
80 Minutes

FOR FACE & BODY

PABA & PARABEN FREE
PHTHALATE FREE
BROAD SPECTRUM

PURE
GENTLE
PLANT
EXTRACTS

3 FL. OZ / 89 ML